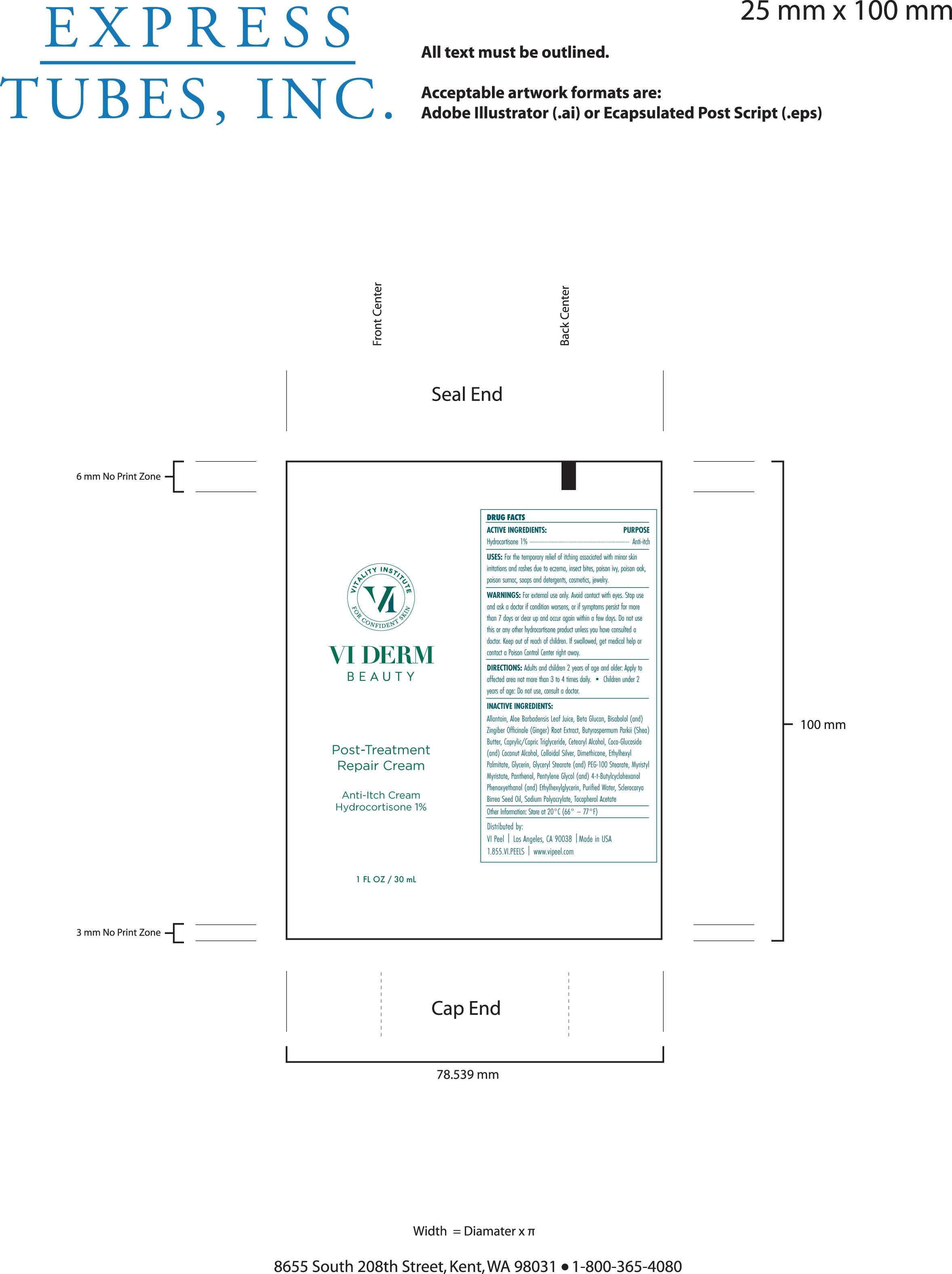 DRUG LABEL: Post-Treatment Repair Cream
NDC: 70484-105 | Form: CREAM
Manufacturer: Vi Medical Products Inc.
Category: otc | Type: HUMAN OTC DRUG LABEL
Date: 20200413

ACTIVE INGREDIENTS: HYDROCORTISONE 1 g/100 mL
INACTIVE INGREDIENTS: .ALPHA.-TOCOPHEROL ACETATE; MEDIUM-CHAIN TRIGLYCERIDES; SCLEROCARYA BIRREA SEED OIL; GINGER; GLYCERYL MONOSTEARATE; MYRISTYL MYRISTATE; ALLANTOIN; ALOE VERA LEAF; PHENOXYETHANOL; LEVOMENOL; CETOSTEARYL ALCOHOL; COCONUT OIL; 4-TERT-BUTYLCYCLOHEXANOL; SHEA BUTTER; ETHYLHEXYL PALMITATE; WATER; GLYCERIN; SODIUM POLYACRYLATE (8000 MW); SILVER; DIMETHICONE; ETHYLHEXYLGLYCERIN; PEG-100 STEARATE; COCO GLUCOSIDE; PANTHENOL; PENTYLENE GLYCOL

Post-Treatment Repair Cream

Active Ingredients: Purpose

Hydrocortisone 1% Anti-itch

PURPOSE

Uses: For the temporary relief of itching associated with minor skin irritations and rashes due to eczema, insect bites, poison ivy, poison oak, poison sumac, soaps and detergents, cosmetics, jewelry.

Keep out of reach of children. If swallowed, get medical help or contact a Poison Control Center right away.

Stop use and ask a doctor if condition worsens, or if symptoms persist for more than 7 days or clear up and occur again within a few days.

WARNINGS

Warnings: For external use only. Avoid contact with eyes. Do not use this or any other hydrocortisone products unless you have consulted a doctor.

DOSAGE AND ADMINISTRATION

Directions: Adults and children under 2 years of age and older: Apply to affected area not more than 3 to 4 times daily.

Children under 2 years of age: Do not use, consult a doctor

Inactive Ingredients:

Allantoin, Aloe Barbadensis Leaf Juice, Beta Glucan, Bisabolol (and)Zingiber Officinale (Ginger) Root Extract, Butyrospermum Parkii (Shea) Butter, Caprylic/Capric Triglyceride, Cetearyl Alcohol, Coco-Glucoside (and) Coconut Alcohol, Colloidal Silver, Dimethicone, Ethylhexyl Palmitate, Glycerin, Glyceryl Stearate (and) PEG-100 Stearate, Myristyl Myristate, Panthenol, Pentylene Glycol (and) 4-t-Butylcyclohexanol Phenoxyethanol (and) Ethylhexylglycerin, Purified Water, Sclerocarya Birrea Seed Oil, Sodium Polyacrylate, Tocopherol Acetate

Other Information: Store at 20°C (66° – 77°F)

PACKAGE LABEL

VI Derm Beauty

Post-Treatment Repair Cream

Anti-itch Cream

Hydrocortisone 1%

1 FL OZ / 30 mL